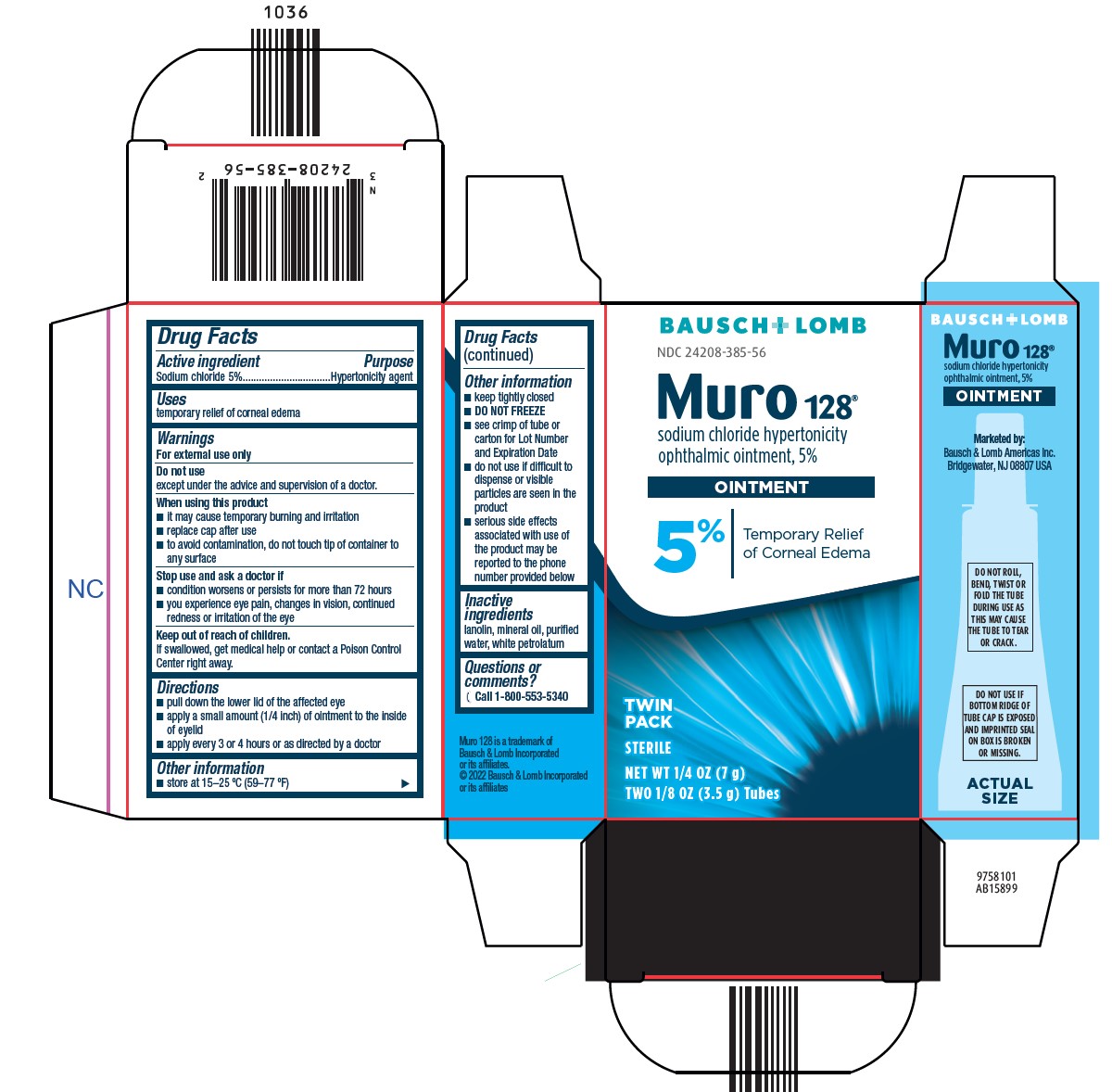 DRUG LABEL: Muro 128
NDC: 24208-385 | Form: OINTMENT
Manufacturer: Bausch & Lomb Incorporated
Category: otc | Type: HUMAN OTC DRUG LABEL
Date: 20240925

ACTIVE INGREDIENTS: SODIUM CHLORIDE 50 mg/1 g
INACTIVE INGREDIENTS: LANOLIN; WATER; PETROLATUM; MINERAL OIL

Muro 128 Drug Facts

Active ingredient

Sodium chloride 5%

Purpose

Hypertonicity agent

Uses

temporary relief of corneal edema

Warnings

For external use only

Do not use
except under the advice and supervision of a doctor.

When using this product

- it may cause temporary burning and irritation
- replace cap after use
- to avoid contamination, do not touch tip of container to any surface

Stop use and ask a doctor if

- condition worsens or persists for more than 72 hours
- you experience eye pain, changes in vision, continued redness or irritation of the eye

Keep out of reach of children.

If swallowed, get medical help or contact a Poison Control Center right away.

Directions

- pull down the lower lid of the affected eye
- apply a small amount (1/4 inch) of ointment to the inside of eyelid
- apply every 3 or 4 hours or as directed by a doctor

Other information

- store at 15-25 °C (59-77 °F)
- keep tightly closed
- DO NOT FREEZE
- see crimp of tube or carton for Lot Number and Expiration Date
- do not use if difficult to dispense or visible particles are seen in the product
- serious side effects associated with use of the product may be reported to the phone number provided below

Inactive ingredients

lanolin, mineral oil, purified water, white petrolatum

Questions or comments?

Call 1-800-553-5340

Package/Label Principal Display Panel

BAUSCH +LOMB

NDC 24208-385-56

Muro 128®

sodium chloride hypertonicity

ophthalmic ointment, 5%

OINTMENT

5%|

Temporary Relief

of Corneal Edema

TWIN

PACK

STERILE

NET WT. 1/4 OZ. (7 g)

TWO 1/8 OZ (3.5 g) Tubes

9758101
AB15899